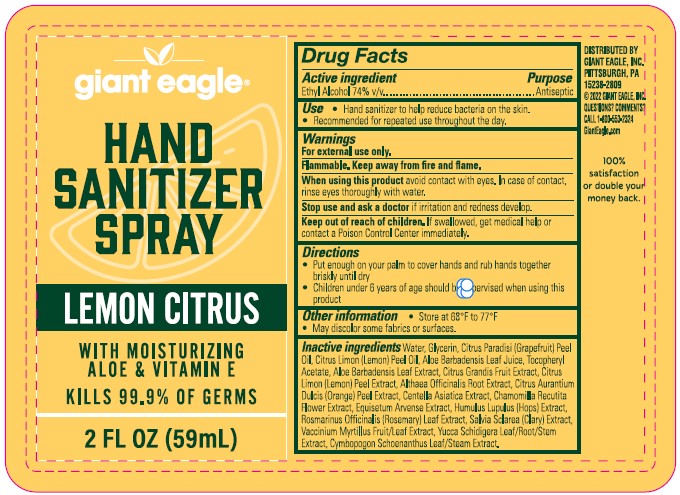 DRUG LABEL: HAND SANITIZER
NDC: 56194-107 | Form: SPRAY
Manufacturer: Giant Eagle, Inc.
Category: otc | Type: HUMAN OTC DRUG LABEL
Date: 20240113

ACTIVE INGREDIENTS: ALCOHOL 74 mL/100 mL
INACTIVE INGREDIENTS: WATER; GLYCERIN; GRAPEFRUIT OIL; LEMON OIL; ALOE VERA LEAF; .ALPHA.-TOCOPHEROL ACETATE; ALTHAEA OFFICINALIS ROOT; CENTELLA ASIATICA; CHAMOMILE; ORANGE PEEL; GRAPEFRUIT PEEL; LEMON PEEL; CYMBOPOGON SCHOENANTHUS WHOLE; EQUISETUM ARVENSE WHOLE; HUMULUS LUPULUS WHOLE; ROSMARINUS OFFICINALIS WHOLE; SALVIA SCLAREA WHOLE; VACCINIUM MYRTILLUS WHOLE; YUCCA SCHIDIGERA

GIANT EAGLE (as PLD) - HAND SANITIZER SPRAY - LEMON CITRUS - 74% EtOH (56194-107)

ACTIVE INGREDIENT

ETHYL ALCOHOL 74%

PURPOSE

ANTISEPTIC

USES

- HAND SANITIZER TO HELP REDUCE BACTERIA ON THE SKIN.
- RECOMMENDED FOR REPEATED USE THROUGHOUT THE DAY.

INACTIVE INGREDIENTS

Giant Eagle - LEMON CITRUS: Water, Glycerin, Citrus Paradisi (Grapefruit) Peel Oil, Aloe Barbadensis Leaf Juice, Tocopheryl Acetate, Aloe Barbadensis Leaf Extract, Citrus Grandis Fruit Extract, Citrus Limon (Lemon) Peel Extract, Althaea Officinalis Root Extract, Citrus Aurantium Dulcis (Orange) Peel Extract, Centella Asiatica Extract, Chamomilla Recutita (Matricaria) Flower Extract, Equisetum Arvense Extract, Humulus Lupulus (Hops) Extract, Rosmarinus Officinalis (Rosemary) Leaf Extract, Salvia Sclarea (Clary) Extract, Vaccinium Myrtillus Fruit/Leaf Extract, Yucca Schidigera Leaf/Root/Stem Extract, Cymbopogon Schoenanthus Leaf/Stem Extract.

WARNINGS

FOR EXTERNAL USE ONLY.

FLAMMABLE. KEEP AWAY FROM FIRE AND FLAME.

WHEN USING THIS PRODUCT, AVOID CONTACT WITH EYES. IN CASE OF CONTACT, RINSE EYES THOROUGHLY WITH WATER.

STOP USE AND ASK A DOCTOR IF IRRITATION AND REDNESS DEVELOP.

KEEP OUT OF REACH OF CHILDREN. IF SWALLOWED, GET MEDICAL HELP OR CONTACT POISON CONTROL CENTER IMMEDIATELY.

DIRECTIONS

- PUT ENOUGH ON YOUR PALM TO COVER HANDS AND RUB HANDS TOGETHER BRISKLY UNTIL DRY.
- CHILDREN UNDER 6 YEARS OF AGE SHOULD BE SUPERVISED WHEN USING THIS PRODUCT.

OTHER INFORMATION

- STORE AT 68°F TO 77°F
- MAY DISCOLOR SOME FABRICS OR SURFACES.